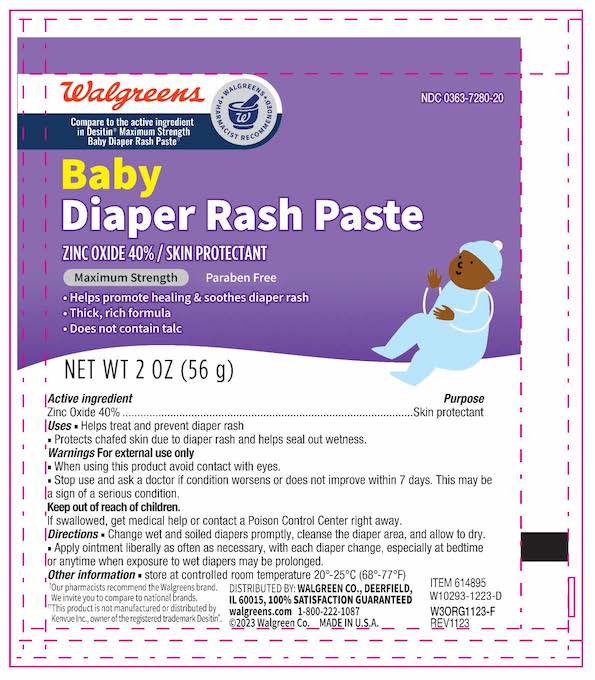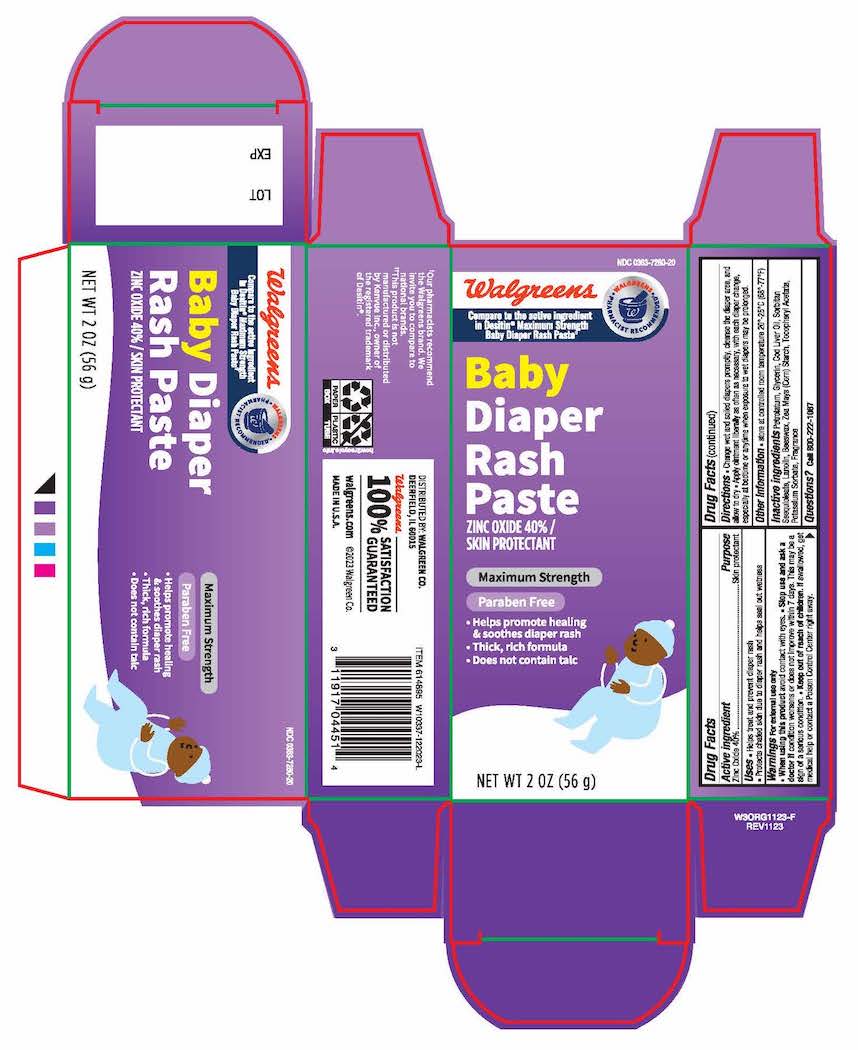 DRUG LABEL: Walgreens Maximum Diaper Rash
NDC: 0363-7280 | Form: OINTMENT
Manufacturer: Walgreens Company
Category: otc | Type: HUMAN OTC DRUG LABEL
Date: 20240507

ACTIVE INGREDIENTS: ZINC OXIDE 400 mg/1 g
INACTIVE INGREDIENTS: PETROLATUM; GLYCERIN; COD LIVER OIL; SORBITAN SESQUIOLEATE; LANOLIN; YELLOW WAX; STARCH, CORN; .ALPHA.-TOCOPHEROL ACETATE; POTASSIUM SORBATE

Active Ingredient

Zinc Oxide 40%

Purposes

Skin protectant

Uses

- helps treat and prevent diaper rash
- protects chafed skin due to diaper rash and helps seal out wetness

Warnings

For external use only

Stop use and ask a doctor if
conditions worsen or does not improve in 7 days. This may be a sign of serious condition.

Directions

- change wet and soiled diapers promptly
- cleanse the diaper area, and allow to dry
- apply ointment liberally as often as necessary, with each diaper change, especially at bedtime or anytime when exposure to wet diapers may be prolonged

Other Information

store at room temperature 20° - 25°C (68° - 77°F)

Inactive ingredients

Petrolatum, Glycerin, Cod liver oil, Sorbitan Seaquloleate, Lanolin, Beeswax, ZeaMays(Corn)Starch, Tocopheryl Acetatate, Potassium Sorbate, Fragrance

Prinical Display panel

Walgreens Baby Diaper Rash Paste NDC 0363-7280-20

Zinc Oxide 40% Skin protectant

Maximum Strength

Paraben free

Does No contain Talc

NEt WT 2 OZ (56g)